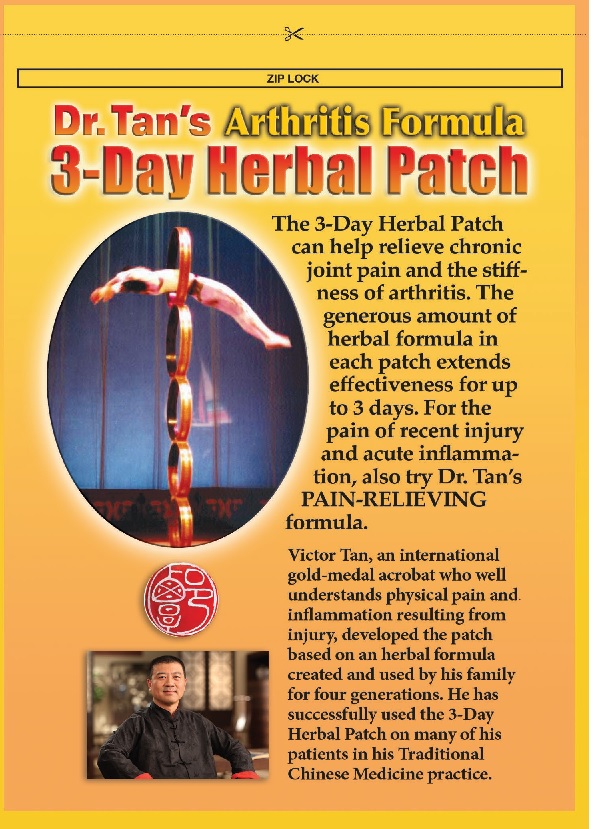 DRUG LABEL: Dr Tans Arthritis Formula   3 day Patch
NDC: 71446-001 | Form: PATCH
Manufacturer: Great Loong LLC
Category: otc | Type: HUMAN OTC DRUG LABEL
Date: 20220113

ACTIVE INGREDIENTS: MENTHOL 0.5 g/1 g
INACTIVE INGREDIENTS: BORNEOL; CARTHAMUS TINCTORIUS FLOWER BUD; DRAGON'S BLOOD; FRANKINCENSE; LIGUSTICUM WALLICHII ROOT; ANGELICA DAHURICA VAR. FORMOSANA ROOT; PAEONIA ANOMALA ROOT; RHEUM OFFICINALE ROOT; SANDALWOOD; SYZYGIUM AROMATICUM LEAF; GLYCERIN; CROSPOVIDONE; POVIDONE K90; SODIUM POLYACRYLATE (8000 MW); SODIUM BENZOATE

Dr Tans Arthritis Formula 3 day Patch

Actives

Menthol 0.5 %

Inactives

Borneol , Carthamus Tinctorious L. , Draconis Sanguis, Frankincense, Ligusticum Walichii, Padix Auklandiae, Radix Angelicae Forrnosanae, Radix Paeoniae Rubra, Rheum Officinale Baillon, Sandalwood, Syzygium Aromaticum, hydrogel.

Purpose

External Analgesic

Indication and Usage

For adults and children 10 and older for the temporary relief of: • chronic arthritis • backache • joint and muscle pain and stiffness • old sports injuries.

Directions

Clean and dry the affected area. Peel film off of patch and apply the herbal-formula side onto the skin. Peel film off the larger dressing patch and apply over the herbal patch to secure it in place. Patch will continue to release herbal formula to the skin for 3 days if desired.

Warnings

• For external use only. • Do not apply to open sores or wounds. • If skin irritation or a rash occurs, remove patch and consult physician. ·Avoid contact with eyes and mucous membranes. • If pregnant or breast feeding, consult a doctor before using.

Keep out of reach of children